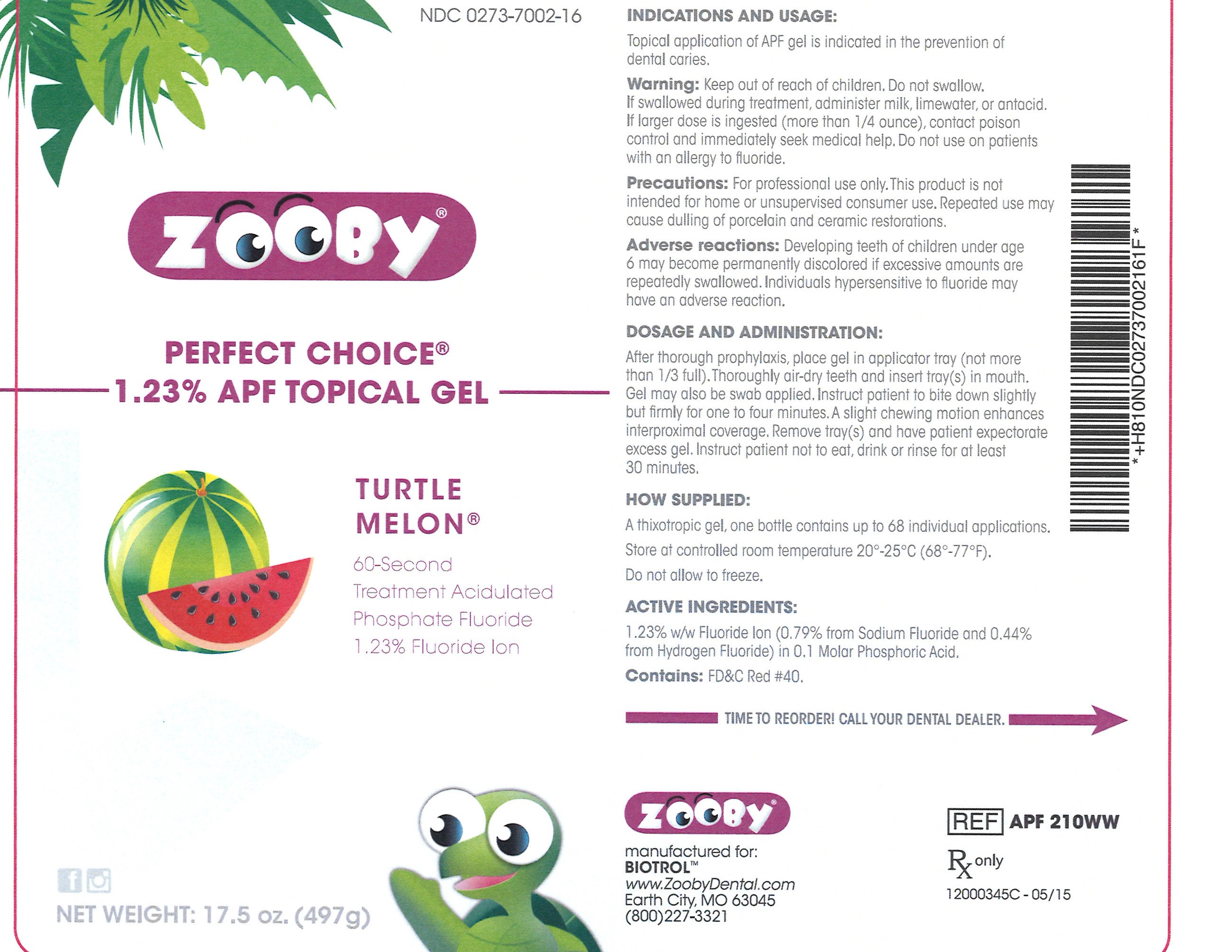 DRUG LABEL: Perfect Choice
NDC: 0273-7002 | Form: GEL
Manufacturer: Young Dental Manufacturing Co 1, LLC.
Category: prescription | Type: HUMAN PRESCRIPTION DRUG LABEL
Date: 20181224

ACTIVE INGREDIENTS: HYDROFLUORIC ACID 4.4 mg/1 g; SODIUM FLUORIDE 7.9 mg/1 g

APF Gel - Watermelon

INDICATIONS AND USAGE:

Topical application of APF gel is indicated in the prevention of dental caries.

Warning:

Keep out of reach of children. Do not swallow.

If swallowed during treatment, administer milk, limewater, or antacid. If larger dose is ingested (more than 1/4 ounce), contact poison control and immediately seek medical help. Do not use on patients with an allergy to fluoride.

Precautions:

For professional use only. This product is not intended for home or unsupervised consumer use. Repeated use may cause dulling of porcelain and ceramic restorations.

Adverse reactions:

Developing teeth of children under age 6 may become permanently discolored if excessive amounts are repeatedly swallowed. Individuals hypersensitive to fluoride may have an adverse reaction.

DOSAGE AND ADMINISTRATION:

After thorough prophylaxis, place gel in applicator tray (not more than 1/3 full). Throughly air-dry teeth and insert tray(s) in mouth. Gel may also be swab applied. Instruct patient to bite down slightly but firmly for one to four minutes. A slight chewing motion enhances coverage interproximally. Remove tray(s) and have patient expectorate excess gel. Instruct patient not to eat, drink or rinse for at least 30 minutes.

HOW SUPPLIED:

A thixotropic gel, one bottle contains up to 68 individual applications. Store at controlled room temperature 20°- 25°C (68°-77°F).

Do not allow to freeze.

ACTIVE INGREDIENTS:

1.23% w/w Fluoride Ion (0.79% from Sodium Fluoride and 0.44% from Hydrogen Fluoride) in 0.1 Molar Phosphoric Acid.

Contains: FD&C Red #40.

Principal Display Panel

NDC 0273-7002-16

ZOOBY

PERFECT CHOICE®

1.23% APF TOPICAL GEL

TURTLE

MELON

60-Second

Treatment Acidulated

Phosphate Fluoride

1.23% Fluroide Ion

Net Weight: 17.5 oz. (497g)